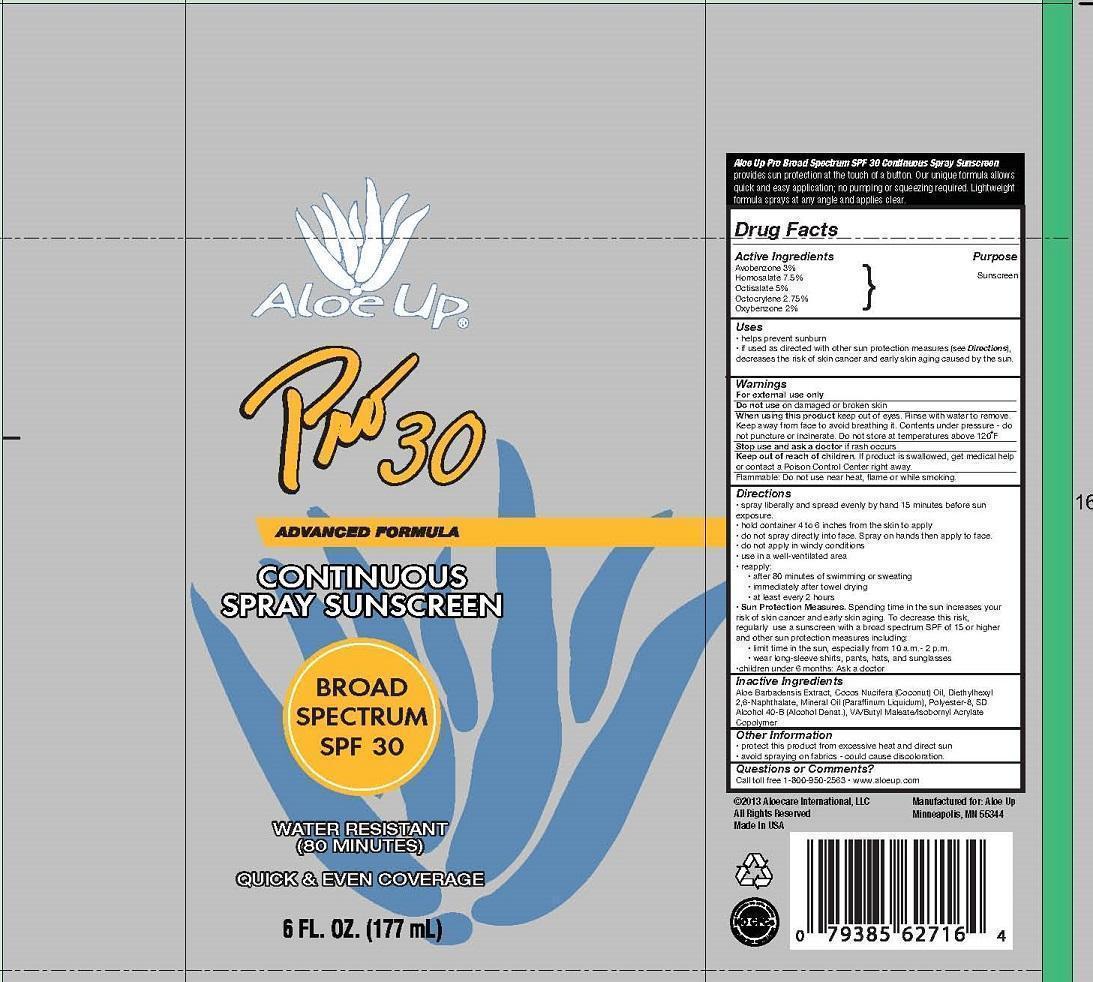 DRUG LABEL: ALOE UP PRO 30
NDC: 61477-209 | Form: SPRAY
Manufacturer: Aloe Care International, LLC
Category: otc | Type: HUMAN OTC DRUG LABEL
Date: 20260128

ACTIVE INGREDIENTS: AVOBENZONE 3 g/100 mL; HOMOSALATE 7.5 g/100 mL; OCTISALATE 5 g/100 mL; OCTOCRYLENE 2.75 g/100 mL; OXYBENZONE 2 g/100 mL
INACTIVE INGREDIENTS: ALOE VERA LEAF; COCONUT OIL; DIETHYLHEXYL 2,6-NAPHTHALATE; MINERAL OIL; POLYESTER-8 (1400 MW, CYANODIPHENYLPROPENOYL CAPPED); ALCOHOL; DIBUTYL MALEATE; ISOBORNYL METHACRYLATE

ALOE UP - PRO SPF 30 SPRAY (61477-209)

ACTIVE INGREDIENTS:

AVOBENZONE (3%)

HOMOSALATE (7.5%)

OCTISALATE (5%)

OCTOCRYLENE (2.75%)

OXYBENZONE (2%)

PURPOSE:

SUNSCREEN

INDICATIONS:

HELPS PREVENT SUNBURN.

DIRECTIONS:

SPRAY LIBERALLY AND SPREAD EVENLY BY HAND 15 MINUTES BEFORE SUN EXPOSURE.

HOLD 4 TO 6 INCHES FROM THE SKIN TO APPLY.

DO NOT SPRAY DIRECTLY INTO FACE. SPRAY ON HANDS THEN APPLY TO FACE.

DO NOT APPLY IN WINDY CONDITIONS.

USE IN A WELL-VENTILATED AREA.

REAPPLY: AFTER 80 MINUTES OF SWIMMING OR SWEATING; IMMEDIATELY AFTER TOWEL DRYING, AT LEAST EVERY 2 HOURS.

KEEP OUT OF REACH OF CHILDREN.

WARNINGS:

FOR EXTERNAL USE ONLY. dO NOT USE ON DAMAGED OR BROKEN SKIN. WHEN USING THIS PRODUCT KEEP OUT OF EYES. RINSE WITH WATER TO REMOVE. KEEP AWAY FROM FACE TO AVOID BREATHING IT. CONTENTS UNDER PRESSURE- DO NOT PUNCTURE OR INCINERATE. DO NOT STORE AT TEMPERATURES ABOUT 120 F. STOP USE AND ASK A DOCTOR IF RASH OCCURS. KEEP OUT OF REACH OF CHILDREN. IF PRODUCT IS SWALLOWED, GET MEDICAL HELP OR CONTACT A POISON CONTROL CENTER RIGHT AWAY. FLAMMABLE: DO NOT USE NEAR HEAT, FLAME OR WHILE SMOKING.

INACTIVE INGREDIENT

Other Ingredients:

ALOE BARBADENSIS EXTRACT, COCOS NUCIFERA (COCONUT) OIL, DIETHYLHEXYL 2,6-NAPHTHALATE, MINERAL OIL (PARAFFINUM LIQUIDUM), POLYESTER-8, SD ALCOHOL 40-B (ALCOHOL DENAT.), VA/BUTYL MALEATE/ISOBORNYL ACRYLATE COPOLYMER